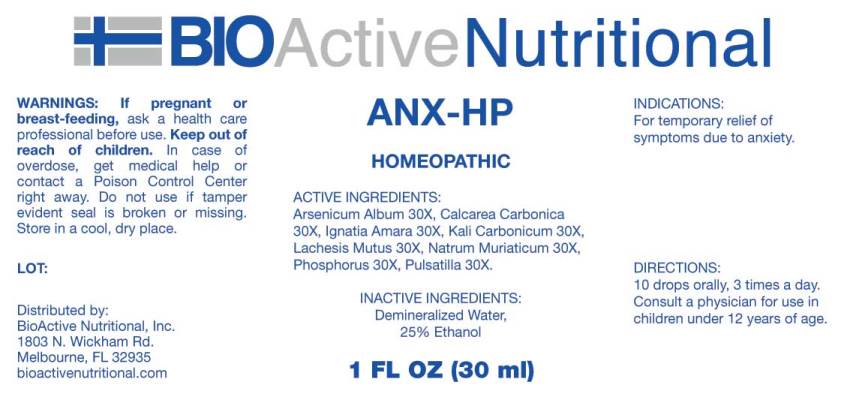 DRUG LABEL: ANX HP
NDC: 43857-0041 | Form: LIQUID
Manufacturer: BioActive Nutritional, Inc.
Category: homeopathic | Type: HUMAN OTC DRUG LABEL
Date: 20170614

ACTIVE INGREDIENTS: ARSENIC TRIOXIDE 30 [hp_X]/1 mL; OYSTER SHELL CALCIUM CARBONATE, CRUDE 30 [hp_X]/1 mL; STRYCHNOS IGNATII SEED 30 [hp_X]/1 mL; POTASSIUM CARBONATE 30 [hp_X]/1 mL; LACHESIS MUTA VENOM 30 [hp_X]/1 mL; SODIUM CHLORIDE 30 [hp_X]/1 mL; PHOSPHORUS 30 [hp_X]/1 mL; PULSATILLA VULGARIS 30 [hp_X]/1 mL
INACTIVE INGREDIENTS: WATER; ALCOHOL

Drug Facts:

ACTIVE INGREDIENTS:

Arsenicum Album 30X, Calcarea Carbonica 30X, Ignatia Amara 30X, Kali Carbonicum 30X, Lachesis Mutus 30X, Natrum Muriaticum 30X, Phosphorus 30X, Pulsatilla 30X.

INDICATIONS:

For temporary relief of symptoms due to anxiety.

WARNINGS:

If pregnant or breast-feeding, ask a health care professional before use.

Keep out of reach of children. In case of overdose, get medical help or contact a Poison Control Center right away.

Do not use if tamper evident seal is broken or missing.

Store in cool, dry place.

DIRECTIONS:

10 drops orally, 3 times a day. Consult a physician for use in children under 12 years of age.

INACTIVE INGREDIENTS:

Demineralized Water, 25% Ethanol.

Keep out of reach of children. In case of overdose, get medical help or contact a Poison Control Center right away.

INDICATIONS:

For temporary relief of symptoms due to anxiety.

QUESTIONS:

Distributed by:

BioActive Nutritional, Inc.

1803 N. Wickham Rd.

Melbourne, FL 32935

bioactivenutritional.com

PACKAGE LABEL DISPLAY:

BIOActive Nutritional

ANX HP

HOMEOPATHIC

1 FL OZ (30 ml)